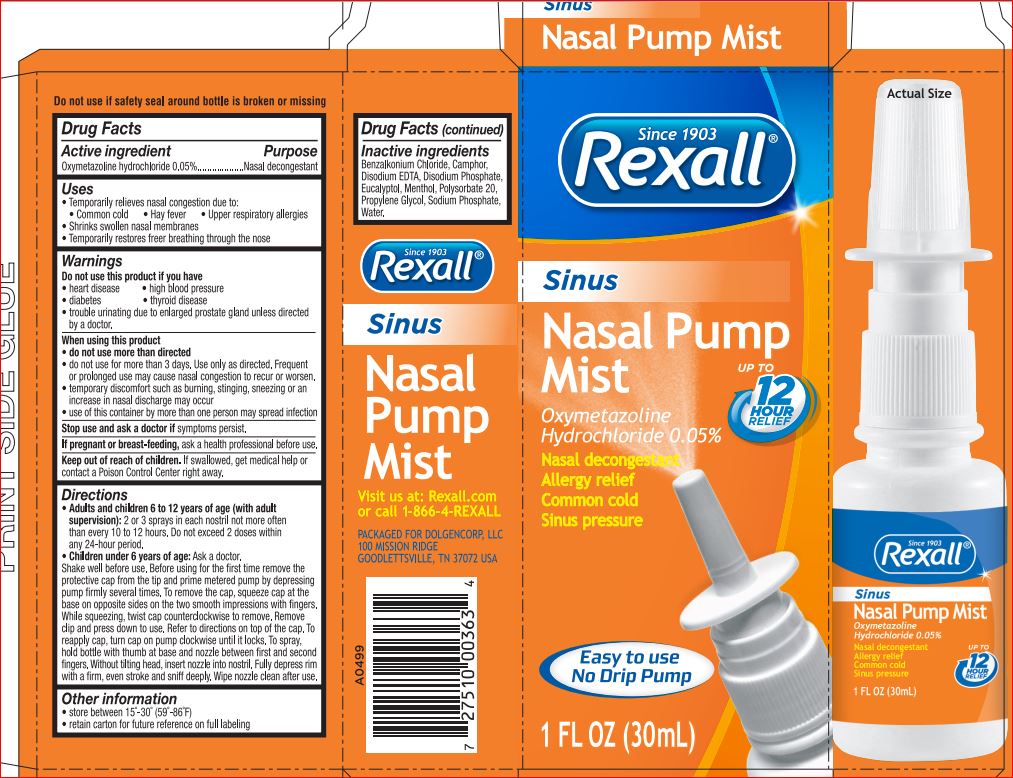 DRUG LABEL: Rexall Sinus Nasal Pump Mist
NDC: 55910-778 | Form: LIQUID
Manufacturer: Dollar General
Category: otc | Type: HUMAN OTC DRUG LABEL
Date: 20171004

ACTIVE INGREDIENTS: Oxymetazoline Hydrochloride 0.05 g/100 mL
INACTIVE INGREDIENTS: Benzalkonium Chloride; CAMPHOR (SYNTHETIC); EDETATE DISODIUM; SODIUM PHOSPHATE, DIBASIC, ANHYDROUS; EUCALYPTOL; Menthol; Polysorbate 20; Propylene Glycol; Sodium Phosphate; Water

DRug Facts

Active ingredients Purpose

Oxymetazoline Hydrochloride 0.05% Nesal Decongestant

Uses

temporarily relief nasal decongestion due to:
- common cold
- hay fever
- upper respiratory allergies
- shrinks swollen membranes
- temporarily restores freer breathing through the nose

Do not use this product if person has heart disease, high blood pressure, thyroid disease, diabetes, or if adult has difficulty in urination due to enlargement of the prostate gland unless directed by a doctor.

When using this product
Do not exceed recommended dosage.
This product may cause temporary discomfort such as burning, stinging, sneezing, or an increase in nasal discharge.

The use of this container by more than one person may spread infection

Stop use and ask doctor if

Symptoms persist

If pregnant or breast-feeding, ask a health professional before use

DOSAGE AND ADMINISTRATION

Directions. Adults and children 6 to under 12 years of age (with adult supervision): 2 or 3 sprays in each nostril not more often than every 10 to 12 hours. Do not exceed 2 doses in any 24-hour period. Children under 6 years of age: consult a doctor

shake well before each use. Before using for the first time remove the protective cap from the tip and prime mitered pump by depressing pump firmly several times. To remove the cap, squeeze cap at the base on opposite sides on the two smooth impressions with fingers. While squeezing, twist cap counterclockwise to remove. Remove clip and press down to use. Refer to directions on top of each cap. To reapply cap, turn cap on pump clockwise until it locks. To spray, hold bottle with thumb at base and nozzle between first and second flingers. Without tilting head, insert nozzle into nostril. Fully depress rim with a firm, even stroke and sniff deeply. Wipe nozzle clean after use.

Inactive ingredients

Benzalkonium Chloride
Camphor
Disodium EDTA
Disodium Phosphate
Eucalyptol
Menthol
Polysorbate 20
Propylene Glycol
Sodium Phosphate
Water